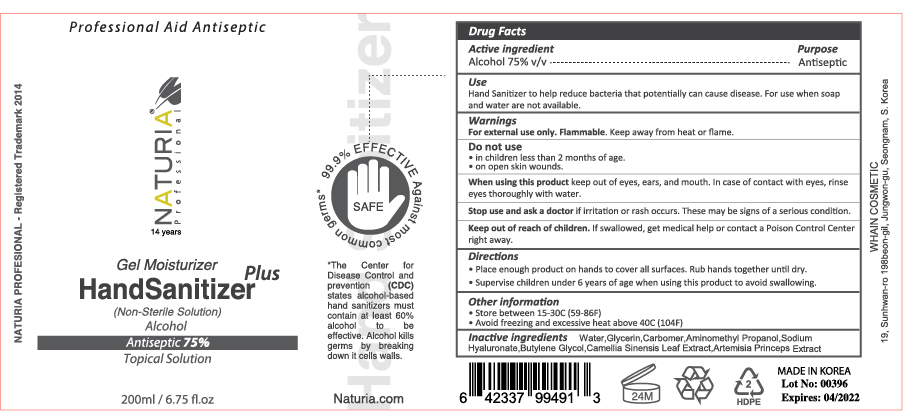 DRUG LABEL: NATURIA Gel Moisturizer Plus HandSanitizer
NDC: 73823-752 | Form: GEL
Manufacturer: WHAIN COSMETIC
Category: otc | Type: HUMAN OTC DRUG LABEL
Date: 20200512

ACTIVE INGREDIENTS: ALCOHOL 150 mL/200 mL
INACTIVE INGREDIENTS: AMINOMETHYL PROPANEDIOL; GLYCERIN; HYALURONATE SODIUM; BUTYLENE GLYCOL; CARBOMER HOMOPOLYMER, UNSPECIFIED TYPE; WATER; ARTEMISIA PRINCEPS LEAF; GREEN TEA LEAF

NATURIA Gel Moisturizer Plus HandSanitizer
200 ml
73823-752-01